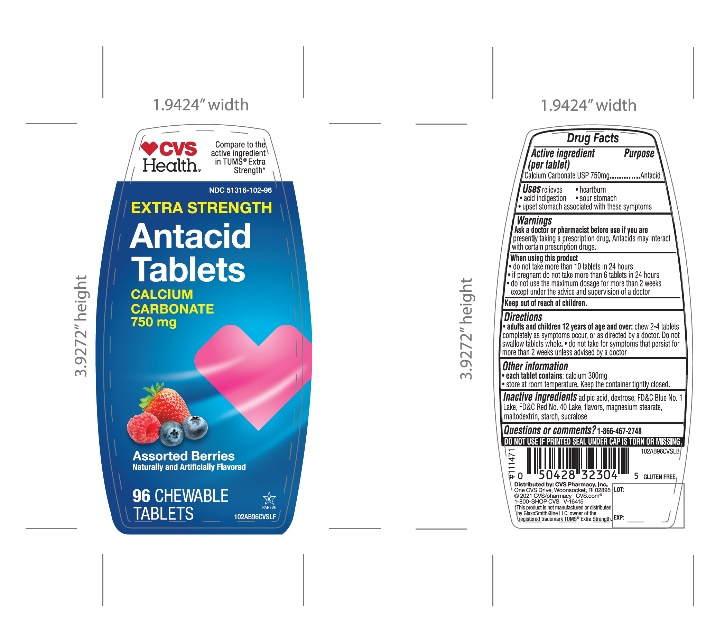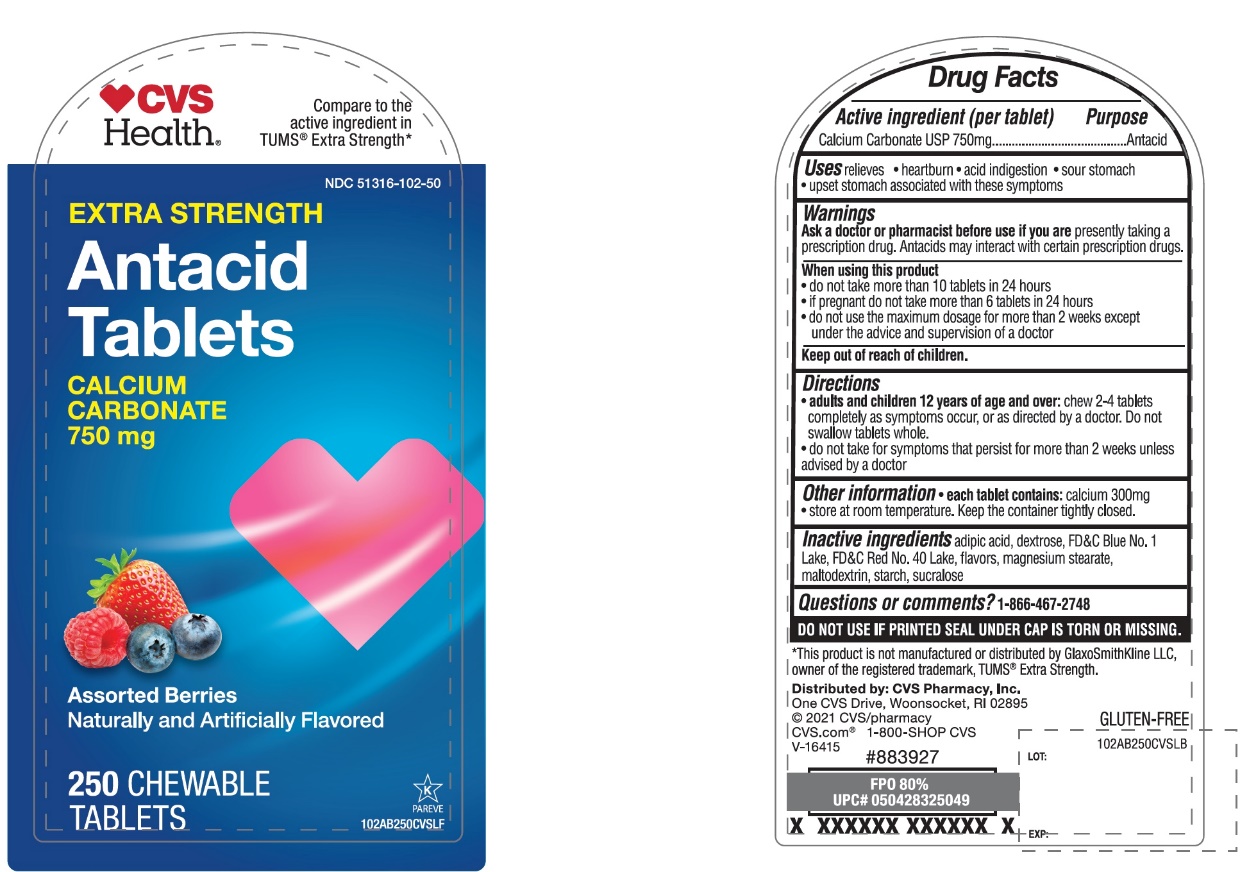 DRUG LABEL: CVS PHARMACY,INC.

NDC: 51316-102 | Form: TABLET, CHEWABLE
Manufacturer: CVS PHARMACY,INC.
Category: otc | Type: HUMAN OTC DRUG LABEL
Date: 20251204

ACTIVE INGREDIENTS: CALCIUM CARBONATE 750 mg/1 1
INACTIVE INGREDIENTS: ADIPIC ACID; DEXTROSE, UNSPECIFIED FORM; FD&C BLUE NO. 1; FD&C RED NO. 40; MAGNESIUM STEARATE; MALTODEXTRIN; STARCH, CORN; SUCRALOSE

CVS Extra Strength Antacid Tablet Drug Facts

Active ingredient

Calcium Carbonate USP 750mg

Purpose

Antacid

Uses

relieves:

• heartburn

• sour stomach

• acid indigestion

• upset stomach associated with these symptoms

Warnings

Ask a doctor or pharmacist before use if you aretaking a prescription drug. Antacids may interact with certain prescription drugs.

When using this product

• do not take more than 10 tablets in 24 hours

• if pregnant do not take more than 6 tablets in 24 hours

• do not use the maximum dosage for more than 2 weeks except under the advice and supervision of a doctor.

Directions

• adults and children 12 years of age and over:chew 2-4 tablets completely as symptoms occur, or as directed by a doctor. Do not swallow tablets whole.

• do not take for symptoms that persist for more than 2 weeks unless advised by a doctor.

Other Information

• each tablets contains:calcium 300mg

• store at room temperature. Keep the container tightly closed

Inactive ingredients

adipic acid, dextrose, FD&C Blue No. 1 Lake, FD&C Red No. 40 Lake, flavors, Magnesium stearate, maltodextrin, starch, sucralose

Questions

1-866-467-2748

SAFETY SEALED: DO NOT USE IF PRINTED SEAL UNDER CAP IS TORN OR MISSING

Package/Label Principal Display Panel

*Compare to the active ingredient in Extra Strength Tums®

NDC 51316-102-96

EXTRA STRENGTH

Antacid Tablets

Calcium Carbonate 750 mg

Fast Relief of Upset Stomach, Heartburn, and Acid Indigestion

Assorted Berries

Naturally and Artificially Flavored

250 Chewable Tablets

Distributed by

*This product is not manufactured or distributed by GlaxoSmithKline LLC, the owner of the registered trademark Extra Strength Tums®

Package Label for 96 Chewable Tablets